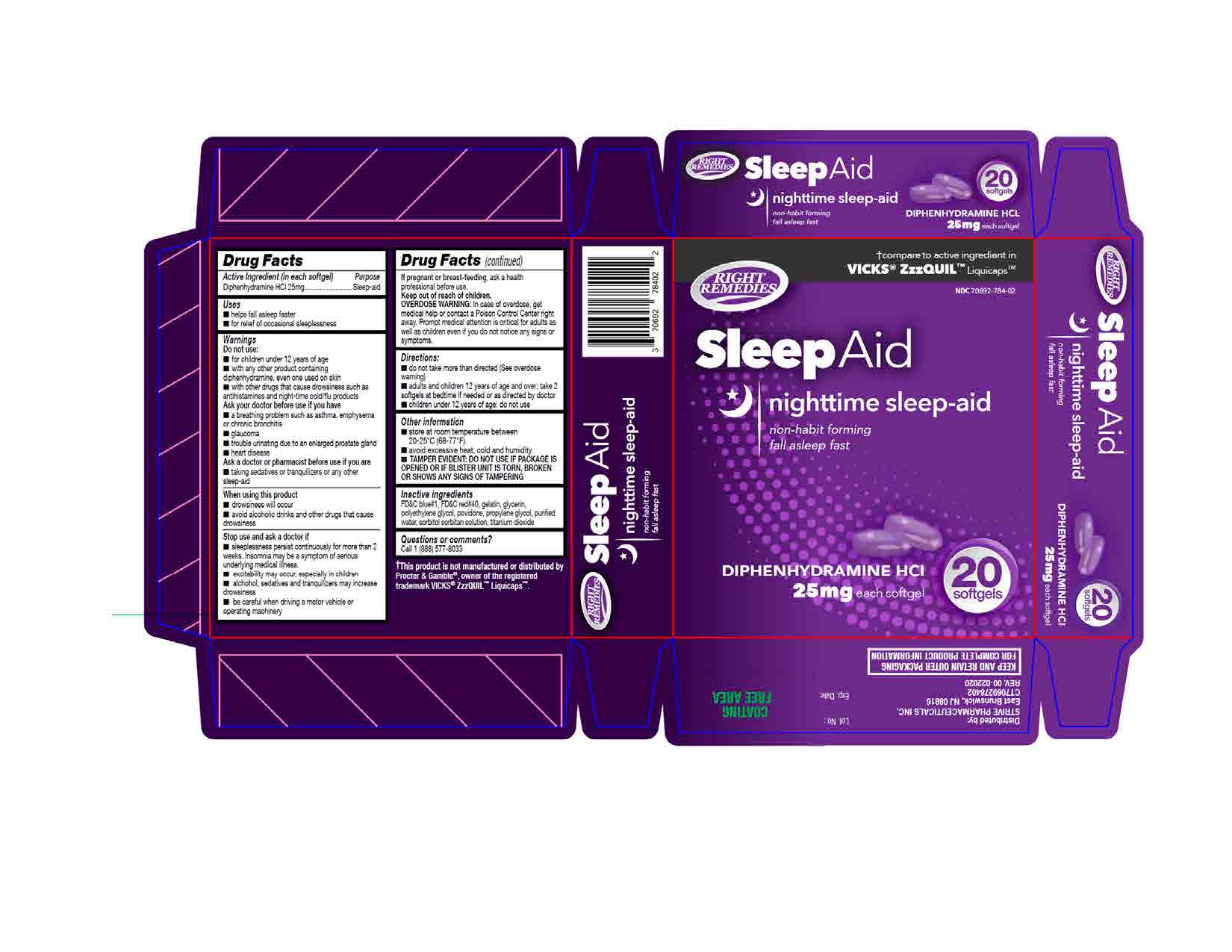 DRUG LABEL: Diphenhydramine Hydrochloride
NDC: 70692-784 | Form: CAPSULE, LIQUID FILLED
Manufacturer: Strive Pharmaceuticals Inc.
Category: otc | Type: HUMAN OTC DRUG LABEL
Date: 20240101

ACTIVE INGREDIENTS: DIPHENHYDRAMINE HYDROCHLORIDE 25 mg/1 1
INACTIVE INGREDIENTS: WATER; FD&C BLUE NO. 1; SORBITAN; POLYETHYLENE GLYCOL 400; SORBITOL; PROPYLENE GLYCOL; GLYCERIN; GELATIN, UNSPECIFIED; POVIDONE K30; FD&C RED NO. 40

Sleep-Aid
Diphenhydramine HCl 25mg (Purple Softgel)

ACTIVE INGREDIENT

Diphenhydramine HCl 25mg

PURPOSE

Sleep-aid

INACTIVE INGREDIENT

polyethylene glycol, propylene glycol, FD&C blue # 1, FD&C red # 40, gelatin, glycerin, sorbitol 70%, povidone, purified water.

DOSAGE AND ADMINISTRATION

- do not take more than directed (see overdose warning)
- adults and children 12 years of age and over: take 2 softgels at bedtime if needed or as directed by doctor
- children under 12 years of age: do not use

INDICATIONS AND USAGE

- helps fall asleep faster
- for relief of occasional sleeplessness

Do not use

- for children under 12 years of age
- with any other product containing diphenhydramine, even one used on skin
- with other drugs that cause drowsiness such as antihistamines and night-time cold/flu products

Ask a doctor before use if you have

- glaucoma
- trouble urinating due to an enlarged prostate gland
- a breathing problem such as asthma, emphysema or chronic bronchitis
- heart disease

Ask a doctor or pharmacist before use if you are taking sedatives or tranquilizers or any other sleep-aid

When using this product

- drowsiness may occur
- avoid alcoholic drinks and other drugs that cause drowsiness

Stop use and ask a doctor if

- sleeplessness persist continuously for more than 2 weeks. Insomnia may be a symptom of serious underlying medical illness.
- excitability may occur, especially in children
- alcohol, sedatives and tranquilizers may increase drowsiness
- be careful when driving a motor vehicle or operating machinery

If pregnant or breast-feeding, ask a health professional before use.

Keep out of reach of children.

OVERDOSAGE

Overdose Warning: In case of overdose, get medical help or contact a Poison Control Center right away. Prompt medical attention is critical for adults as well as children even if you do not notice any signs or symptoms.

OTHER SAFETY INFORMATION

- store at room temperature between 20-25°C (68-77ºF).
- avoid excessive heat, cold and humidity.
- TAMPER EVIDENT: DO NOT USE IF PACKAGE IS OPENED OR IF BLISTER UNIT IS TORN, BROKEN OR SHOWS ANY SIGNS OF TAMPERING.